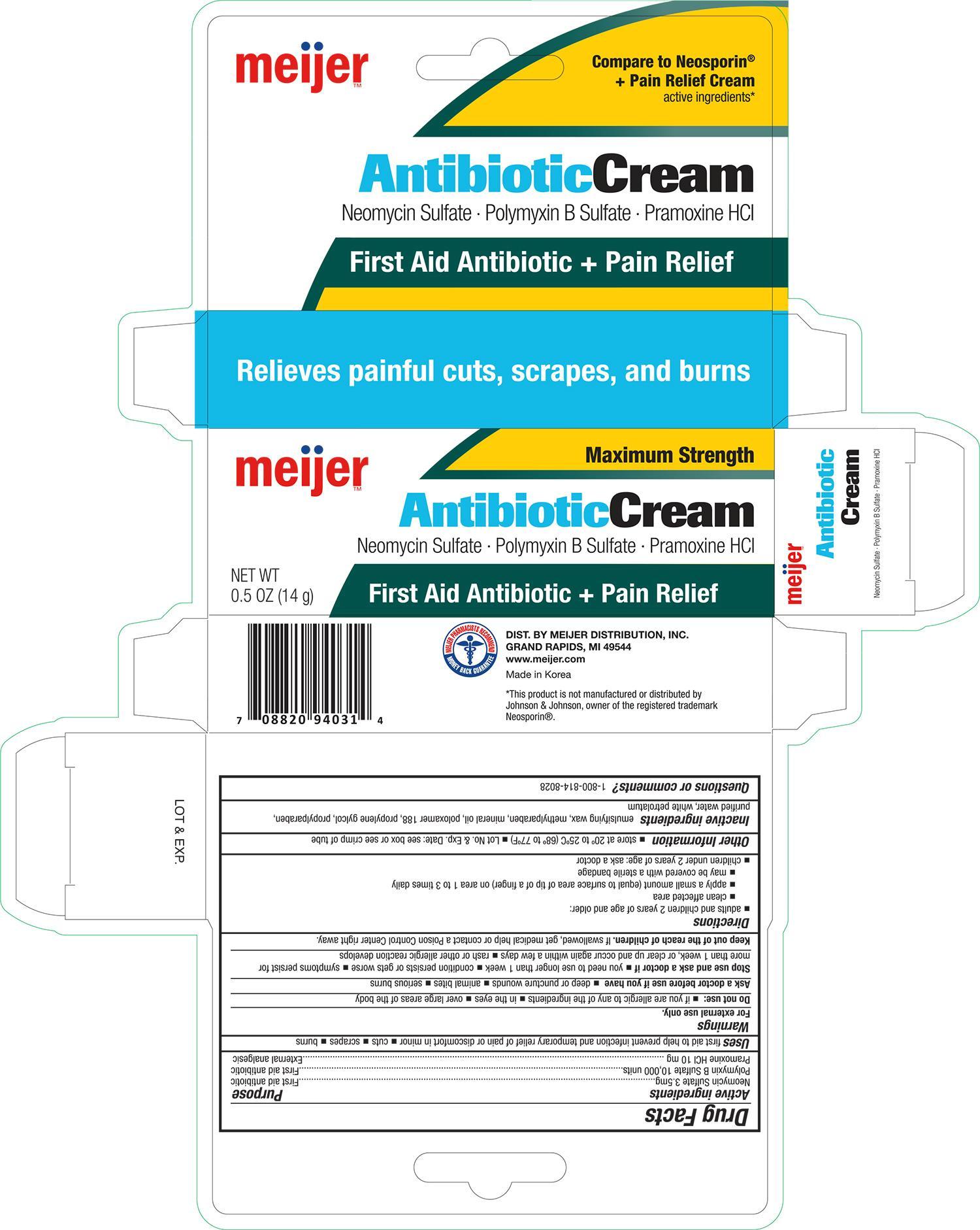 DRUG LABEL: Meijer Antibiotic Plus Pain Relief
NDC: 41250-943 | Form: CREAM
Manufacturer: Meijer, Inc.
Category: otc | Type: HUMAN OTC DRUG LABEL
Date: 20171212

ACTIVE INGREDIENTS: NEOMYCIN SULFATE 3.5 mg/1 g; POLYMYXIN B SULFATE 10000 [USP'U]/1 g; PRAMOXINE HYDROCHLORIDE 10 mg/1 g
INACTIVE INGREDIENTS: METHYLPARABEN; MINERAL OIL; POLOXAMER 188; PROPYLENE GLYCOL; PROPYLPARABEN; WATER; PETROLATUM

Meijer Antibiotic Plus Pain Relief Cream 0.5 oz NBE Neosporin

Active ingredients Purpose

Neomycin Sulfate 3.5 mg............................................................ First aid antibiotic

Polymyxin B Sulfate 10,000 units................................................. First aid antibiotic

Pramoxine HCI 10 mg................................................................. External analgesic

Uses

first aid to help prevent infection and temporary relief of pain or discomfort in minor

- cuts
- scrapes
- burns

Warnings

For external use only

Do not use:

- if you are allergic to any of the ingredients
- in the eyes
- over large areas of the body

Ask a doctor before use if you have

- deep or puncture wounds
- animal bites
- serious burns

Stop use and ask a doctor if

- you need to use longer than 1 week
- condition persits or gets worse
- symptoms persist for more than 1 week, or clear up and occur again within a few days
- rash or other allergic reaction develops

KEEP OUT OF REACH OF CHILDREN

Keep out of the reach of children. If swallowed, get medical help or contact a Poison Control Center right away.

Directions

- adults and children 2 years of age and older:
- clean affeted area
- apply a small amount (equal to surface area of tip of a finger) on area 1 to 3 times daily
- may be covered with a sterile bandage
- children under 2 yeras of age: ask a doctor

Other information

- store at 20° to 25°C (68° to 77°F)
- Lot No. & Exp. Date: see box or see crimp of tube

Inactive ingredients

emulsifying wax, methylparaben, mineral oil, poloxamer 188, propylene glycol, propylparaben, purified water, white petrolatum

DOSAGE AND ADMINISTRATION

DISTRIBUTED BY:

MEIJER DISTRIBUTION, INC.

GRAND RAPIDS, MI 49544

www.meijer.com

MADE IN KOREA